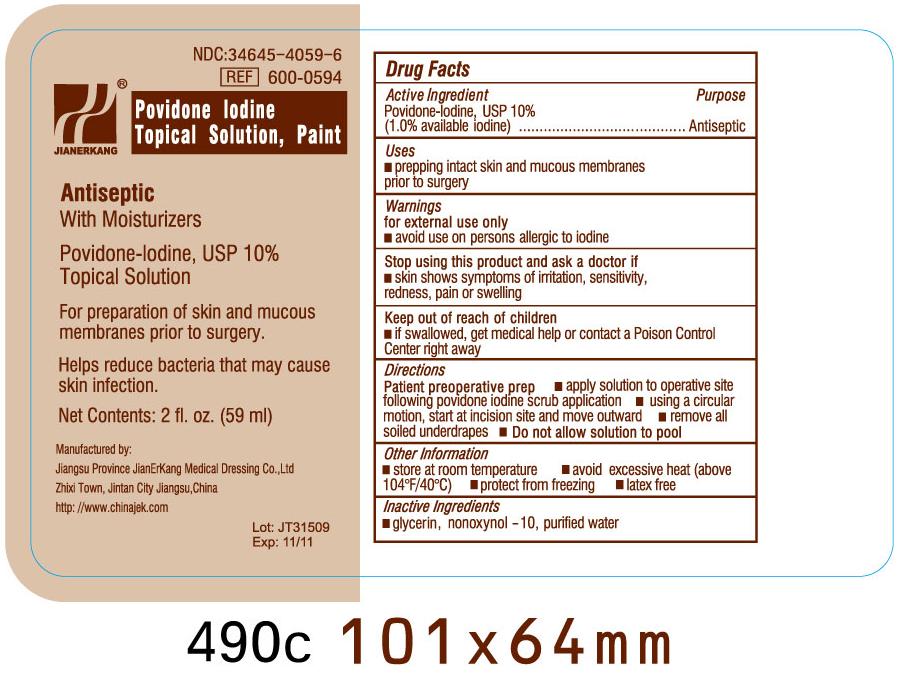 DRUG LABEL: Povidone Iodine
NDC: 34645-4059 | Form: SOLUTION
Manufacturer: Jianerkang Medical Co., Ltd
Category: otc | Type: HUMAN OTC DRUG LABEL
Date: 20231023

ACTIVE INGREDIENTS: POVIDONE-IODINE 10 mg/1 mL
INACTIVE INGREDIENTS: GLYCERIN; NONOXYNOL-10; WATER

Drug Facts

Active Ingredients

Povidone Iodine 10%

Purpose

Antiseptic

Uses

prepping intact skin and mucous membranes prior to surgery

Warnings

For external use only

Avoid use on persons allergic to iodine

STOP USE

Stop using this product and ask a doctor if

Skin shows symptoms of irritation, sensitivity, redness, pain or swelling

Keep out of reach of children

If swallowed, get medical help or contact Poison Control Center right away

Directions

Patient preoperative prep

apply solution to operative site following povidone iodine scrub application

using a circular motion, start at incision site and move outward

remove all soiled underdrapes

Do not allow solution to pool

Other information

store at room temperature avoid excessive heat (above 104oF/40oC) protect from freezing latex free

Inactive Ingredients

Glycerin, Nonoxynol - 10, Purified Water